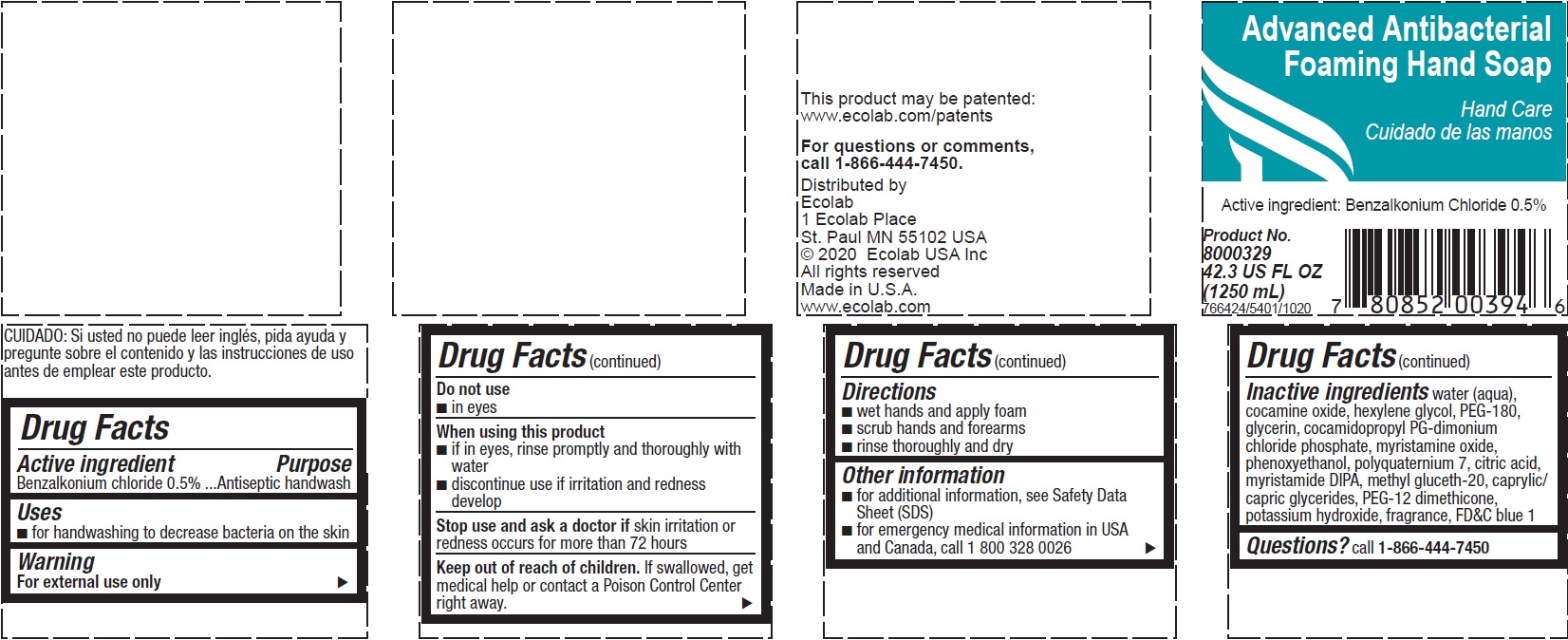 DRUG LABEL: PureForce
NDC: 47593-568 | Form: SOLUTION
Manufacturer: Ecolab Inc.
Category: otc | Type: HUMAN OTC DRUG LABEL
Date: 20240801

ACTIVE INGREDIENTS: BENZALKONIUM CHLORIDE 5 mg/1 mL
INACTIVE INGREDIENTS: FD&C BLUE NO. 1; POTASSIUM HYDROXIDE; PEG-12 DIMETHICONE (300 CST); GLYCERYL MONO- AND DICAPRYLOCAPRATE; METHYL GLUCETH-20; MYRISTIC DIISOPROPANOLAMIDE; ANHYDROUS CITRIC ACID; POLYQUATERNIUM-7 (70/30 ACRYLAMIDE/DADMAC; 1600000 MW); PHENOXYETHANOL; MYRISTAMINE OXIDE; COCAMIDOPROPYL PG-DIMONIUM CHLORIDE PHOSPHATE; GLYCERIN; POLYETHYLENE GLYCOL 8000; HEXYLENE GLYCOL; WATER; COCAMINE OXIDE

Drug Facts

Active Ingredient

Benzalkonium chloride 0.5%

Purpose

Antiseptic handwash

Uses

- for handwashing to decrease bacteria on the skin

Warning

For external use only

Do not use

- in eyes

When using the product

- if in eyes, rinse promptly and thoroughly with water
- discontinue use if irritation and redness develop

Stop use and ask a doctor if skin irritation or redness occurs for more than 72 hours

Keep out of reach of children. If swallowed, get medical help or contact a Poison Control Center right away.

Directions

- wet hands and apply foam
- scrub hands and forearms
- rinse thoroughly and dry

Other information

- for additional information, see Safety Data Sheet (SDS)
- for emergency medical information in USA and Canada, call 1 800 328 0026

INACTIVE INGREDIENT

Inactive ingredients water (aqua), cocamine oxide, hexylene glycol, PEG-180, glycerin, cocamidopropyl PG-dimonium chloride phosphate, myristamine oxide, phenoxyethanol, polyquaternium 7, citric acid, myristamide DIPA, methyl gluceth-20, caprylic/capric glycerides, PEG-12 dimethicone, potassium hydroxide, fragrance, FD&C blue 1

Questions? call 1-866-444-7450

Principal display panel and representative label

Advanced Antibacterial Foaming Hand Soap

Hand Care

Active ingredient: Benzalkonium Chloride 0.5%

Product No.

8000329

42.3 US FL OZ

(1250 mL)

766424/5401/1020

Distributed by

Ecolab

1 Ecolab Place

St. Paul MN 55102 USA

© 2020 Ecolab USA Inc

All rights reserved

Made in U.S.A.

www.ecolab.com